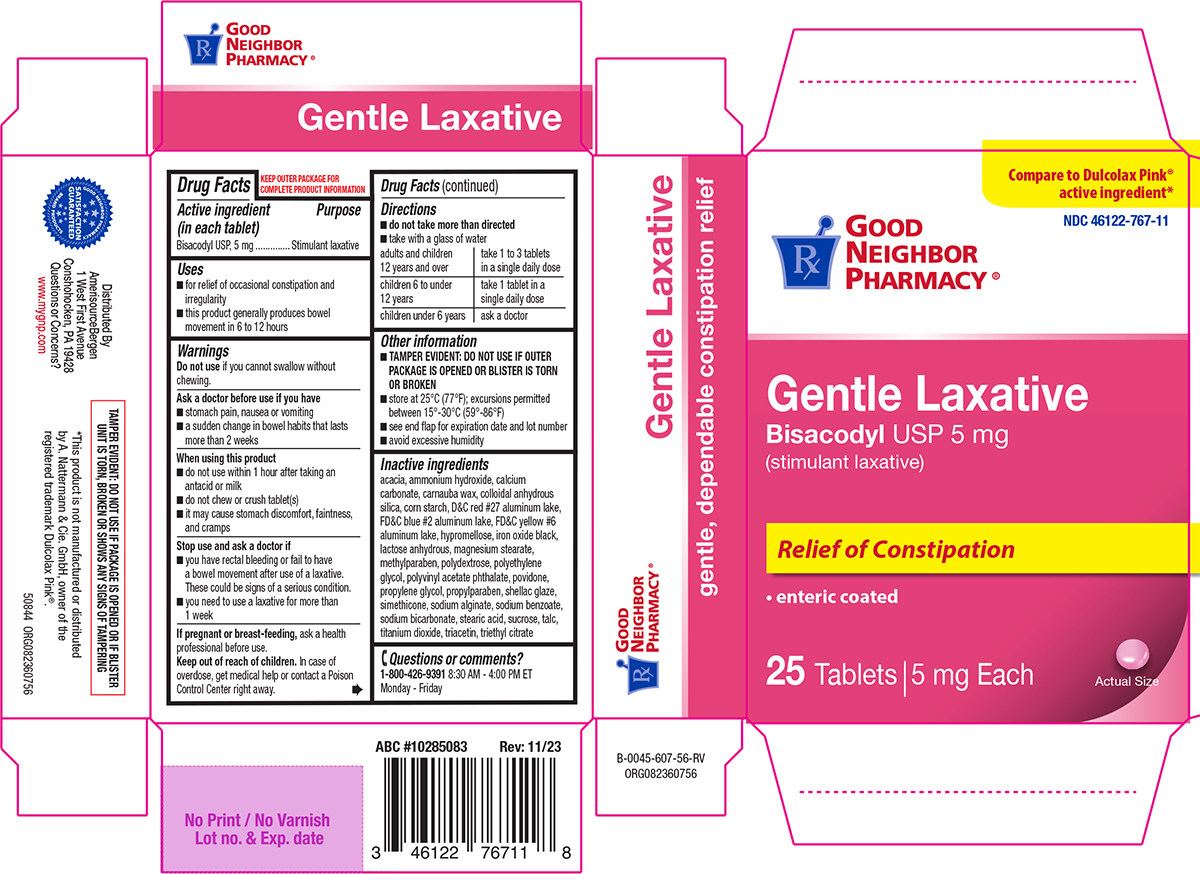 DRUG LABEL: Gentle Laxative
NDC: 46122-767 | Form: TABLET, DELAYED RELEASE
Manufacturer: Amerisource Bergen
Category: otc | Type: HUMAN OTC DRUG LABEL
Date: 20260225

ACTIVE INGREDIENTS: BISACODYL 5 mg/1 1
INACTIVE INGREDIENTS: ACACIA; AMMONIA; CALCIUM CARBONATE; CARNAUBA WAX; SILICON DIOXIDE; STARCH, CORN; D&C RED NO. 27 ALUMINUM LAKE; FD&C BLUE NO. 2 ALUMINUM LAKE; FD&C YELLOW NO. 6 ALUMINUM LAKE; HYPROMELLOSE, UNSPECIFIED; FERROSOFERRIC OXIDE; ANHYDROUS LACTOSE; MAGNESIUM STEARATE; METHYLPARABEN; POLYDEXTROSE; POLYETHYLENE GLYCOL, UNSPECIFIED; Polyvinyl Acetate Phthalate; POVIDONE, UNSPECIFIED; PROPYLENE GLYCOL; PROPYLPARABEN; SHELLAC; DIMETHICONE; WATER; SODIUM ALGINATE; SODIUM BENZOATE; SODIUM BICARBONATE; STEARIC ACID; SUCROSE; TALC; TITANIUM DIOXIDE; TRIACETIN; TRIETHYL CITRATE

Good Neighbor Pharmacy 44-607 Gentle

Active ingredient (in each tablet)

Bisacodyl USP, 5 mg

Purpose

Stimulant laxative

Uses

- for relief of occasional constipation and irregularity
- this product generally produces bowel movement in 6 to 12 hours

Warnings

Do not use

if you cannot swallow without chewing.

Ask a doctor before use if you have

- stomach pain, nausea or vomiting
- a sudden change in bowel habits that lasts more than 2 weeks

When using this product

- do not use within 1 hour after taking an antacid or milk
- do not chew or crush tablet(s)
- it may cause stomach discomfort, faintness, and cramps

Stop use and ask a doctor if

- you have rectal bleeding or fail to have a bowel movement after use of a laxative. These could be signs of a serious condition.
- you need to use a laxative for more than 1 week

If pregnant or breast-feeding,

ask a health professional before use.

Keep out of reach of children.

In case of overdose, get medical help or contact a Poison Control Center right away.

Directions

- do not take more than directed
- take with a glass of water

adults and children 12 years and over | take 1 to 3 tablets in a single daily dose
children 6 to under 12 years | take 1 tablet in a single daily dose
children under 6 years | ask a doctor

Other information

- TAMPER EVIDENT: DO NOT USE IF OUTER PACKAGE IS OPENED OR BLISTER IS TORN OR BROKEN
- store at 25°C (77°F); excursions permitted between 15°-30°C (59°-86°F)
- see end flap for expiration date and lot number
- avoid excessive humidity

Inactive ingredients

acacia, ammonium hydroxide, calcium carbonate, carnauba wax, colloidal anhydrous silica, corn starch, D&C red #27 aluminum lake, FD&C blue #2 aluminum lake, FD&C yellow #6 aluminum lake, hypromellose, iron oxide black, lactose anhydrous, magnesium stearate, methylparaben, polydextrose, polyethylene glycol, polyvinyl acetate phthalate, povidone, propylene glycol, propylparaben, shellac glaze, simethicone, sodium alginate, sodium benzoate, sodium bicarbonate, stearic acid, sucrose, talc, titanium dioxide, triacetin, triethyl citrate

Questions or comments?

1-800-426-9391 8:30 AM - 4:00 PM ET Monday - Friday

Principal Display Panel

GOOD
NEIGHBOR
PHARMACY®

Compare to Dulcolax Pink®
active ingredient*

NDC 46122-767-11

Gentle Laxative
Bisacodyl USP 5 mg
(stimulant laxative)

Relief of Constipation
• enteric coated

25 Tablets | 5 mg Each

Actual Size

GOOD NEIGHBOR PHARMACY BRAND PRODUCTS
SATISFACTION GUARANTEED

Distributed By
AmerisourceBergen
1 West First Avenue
Conshohocken, PA 19428
Questions or Concerns?
www.mygnp.com

TAMPER EVIDENT: DO NOT USE IF PACKAGE IS OPENED OR IF BLISTER
UNIT IS TORN, BROKEN OR SHOWS ANY SIGNS OF TAMPERING

*This product is not manufactured or distributed
by A. Nattermann & Cie. GmbH, owner of the
registered trademark Dulcolax Pink®.

50844 ORG082360756

GNP 44-607